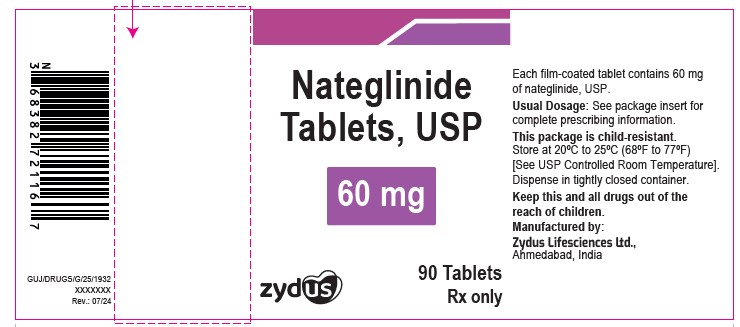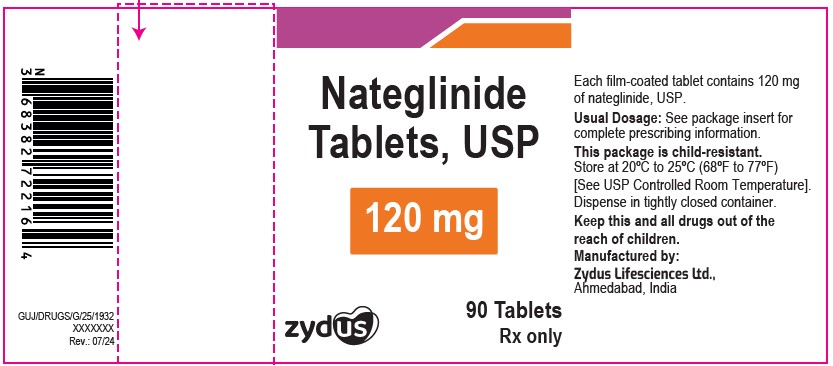 DRUG LABEL: Nateglinide
NDC: 70771-1015 | Form: TABLET, FILM COATED
Manufacturer: Zydus Lifesciences Limited
Category: prescription | Type: HUMAN PRESCRIPTION DRUG LABEL
Date: 20241203

ACTIVE INGREDIENTS: NATEGLINIDE 60 mg/1 1
INACTIVE INGREDIENTS: ANHYDROUS CITRIC ACID; SILICON DIOXIDE; STARCH, CORN; CROSPOVIDONE; HYPROMELLOSES; LACTOSE MONOHYDRATE; MAGNESIUM STEARATE; POLYSORBATE 80; POLYETHYLENE GLYCOL, UNSPECIFIED; POVIDONE; TALC; TITANIUM DIOXIDE

NATEGLINIDE TABELTS

PACKAGE LABEL.PRINCIPAL DISPLAY PANEL

NDC 70771-1015-9 in bottle of 90 tablets

Nateglinide Tablets USP, 60 mg

Rx only

90 tablets

NDC 70771-1016-9 in bottle of 90 tablets

Nateglinide Tablets USP, 120 mg

Rx only

90 tablets